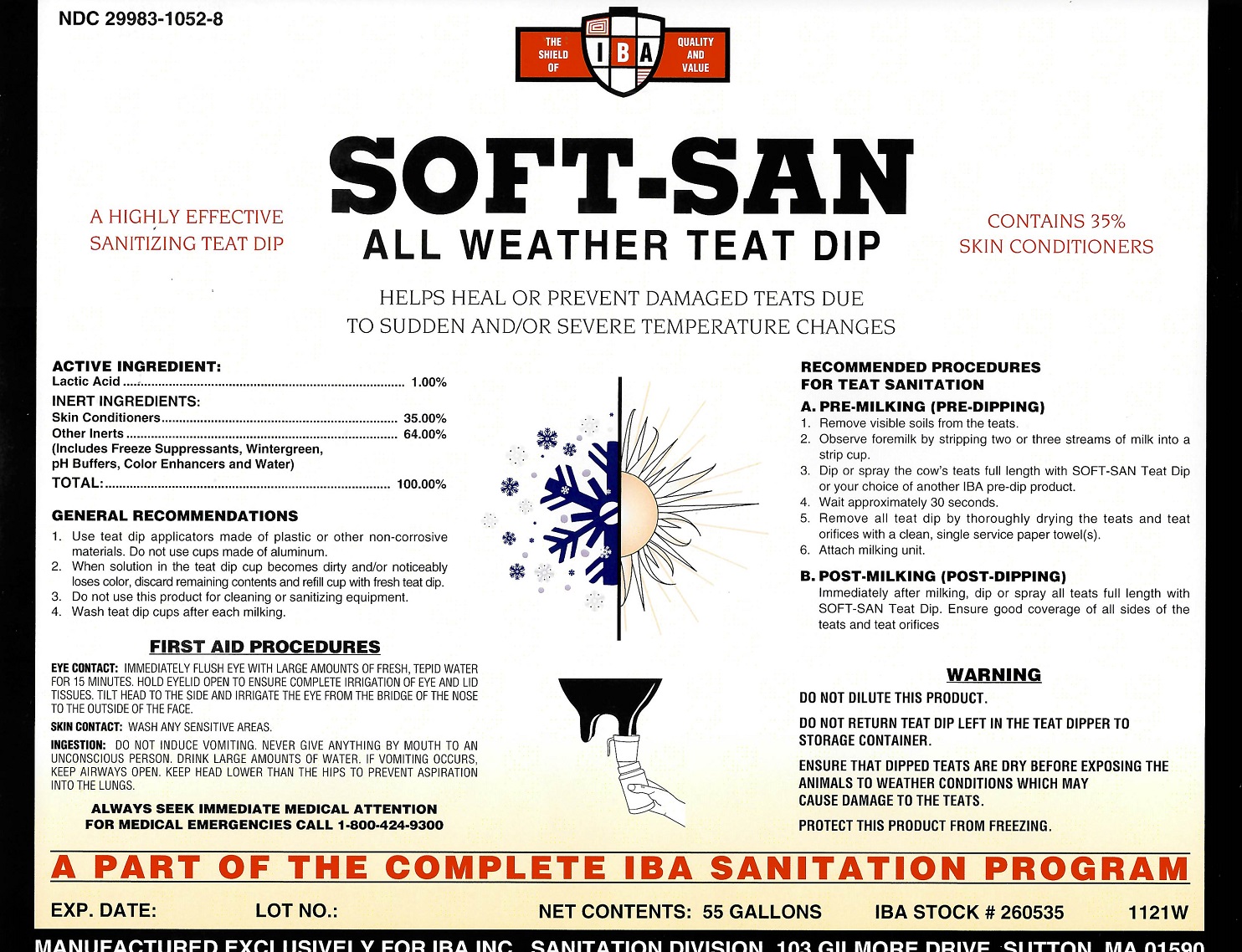 DRUG LABEL: Soft-San
NDC: 29983-1052 | Form: LIQUID
Manufacturer: IBA
Category: animal | Type: OTC ANIMAL DRUG LABEL
Date: 20251211

ACTIVE INGREDIENTS: LACTIC ACID 1 kg/100 kg

SOFT-SAN

ACTIVE INGREDIENTS:

Lactic Acid....................................................................1.00%

INERT INGREDIENTS

Skin Conditioners..........................................................35.00%

Other Inerts..................................................................64.00%

(Includes Freeze Suppressants, Wintergreen,

pH Buffers, Color Enhancers and Water)

Total...........................................................................100.00%

GENERAL RECOMMENDATIONS

1. Use teat dip applicators made of plastic or other

non-corrosive materials. Do not use cups made of aluminum.

2. When solution in teat dip cupbecomes dirty and/or

noticeably loses color, discard remaining contents and refill

cup with fresh teat dip.

3. Do not use this product for cleaning or sanitizing equipment.

4. Wash teat dip cups after each milking.

FIRST AID PROCEDURES

EYE CONTACT: iMMEDIATELY FLUSH EYE LARGE AMOUNTS OF FRESH, TEPID WATER FOR 15 MINUTES. HOLD EYELID OPEN TO ENSURE COMPLETE IRRIGATION OF EYE AND LID TISSUES. TILT HEAD TO THE SIDE AND IRRIGATE THE EYE FROM THE BRIDGE OF THE NOSE TO THE OUTSIDE OF THE FACE.

SKIN CONTACT: WASH ANY SENSITIVE AREAS.

INGESTION: DO NOT INDUCE VOMITING.NEVER GIVE ANYTHING BY MOUTH TO AN UNCONSCIOUS PERSON. DRINK LARGE AMOUNTS OF WATER. IF VOMITING OCCURS, KEEP AIRWAYS OPEN. KEEP HEAD LOWER THAN THE HIPS TO PREVENT ASPIRATION INTO THE LUNGS.

RECOMMENDED PROCEDURES FOR TEAT SANITATION

A. PRE-MILKING (PRE-DIPPING)

1. Remove visible soils from the teats.

2. Observe foremilk by stripping two or three streams of milk into a strip cup.

3. Dip or spray the cow's teats full length with Soft-San Teat Dip or your choice of another IBA pre-dip product.

4. Wait approximately 30 seconds.

5. Remove all teat dip by thoroughly drying the teats and teat orifices with a clean, single service paper towel(s).

6. Attach milking unit.

B. POST-MILKING (POST-DIPPING)

Immediately after milking, dip or spray all teats full length with SOFT-SAN Teat Dip. Ensure good coverage of all sides of the teats and teat orifices.

WARNING

DO NOT DILUTE THIS PRODUCT.

DO NOT RETURN TEA DIP LEFT IN THE TEAT DIPPER TO STORAGE CONTAINER.

ENSURE THAT DIPPED TEATS ARE DRY BEFORE EXPOSING THE ANIMALS TO WEATHER CONDITIONS WHICH MAY CAUSE DAMAGE TO THE TEATS.

PROTECT THIS PRODUCT FROM FREEZING.